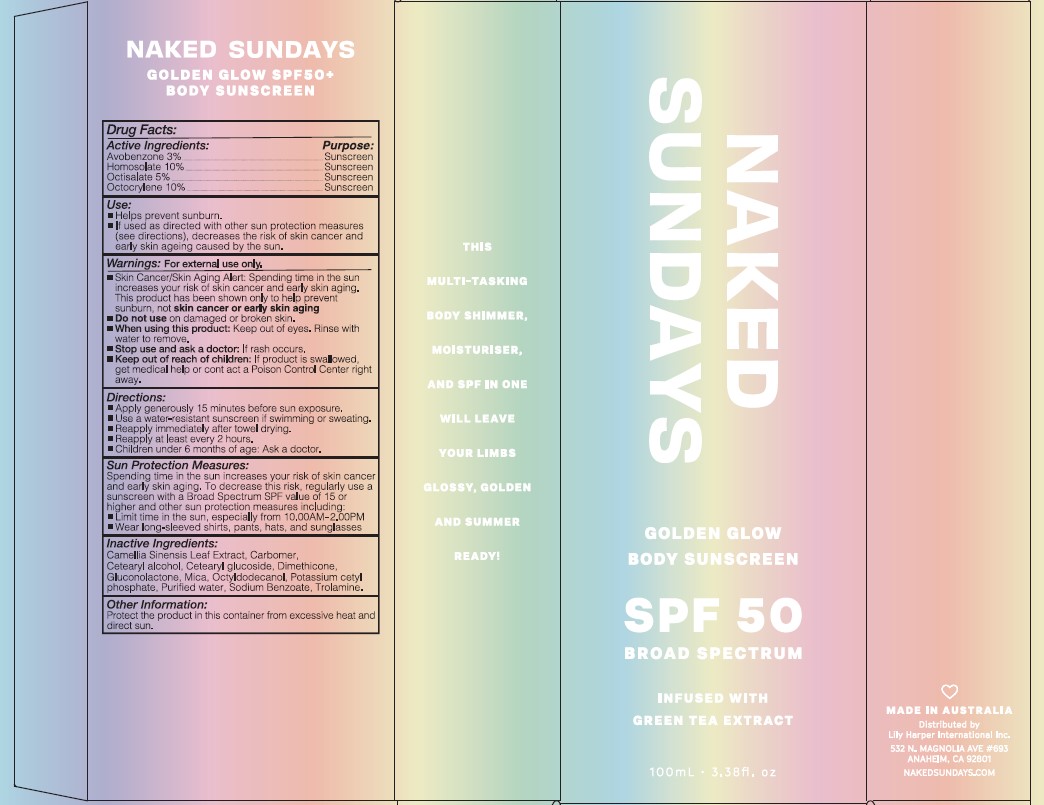 DRUG LABEL: Naked Sundays Golden Glow Body Sunscreen SPF50 100ml
NDC: 81104-500 | Form: CREAM
Manufacturer: NAKED SUNDAYS PTY LTD
Category: otc | Type: HUMAN OTC DRUG LABEL
Date: 20250323

ACTIVE INGREDIENTS: AVOBENZONE 3 g/100 mL; OCTISALATE 5 g/100 mL; HOMOSALATE 10 g/100 mL; OCTOCRYLENE 10 g/100 mL
INACTIVE INGREDIENTS: OCTYLDODECANOL; TROLAMINE; CETOSTEARYL ALCOHOL; CAMELLIA SINENSIS WHOLE; CARBOMER 940; GLUCONOLACTONE; POTASSIUM CETYL PHOSPHATE; WATER; CETEARYL GLUCOSIDE; DIMETHICONE; MICA; SODIUM BENZOATE

Naked Sundays Golden Glow Body Sunscreen SPF50 100ml

Active Ingredients

Avobenzone 3 %

Homosolate 10%

octisalate 5 %

Octocrylene 10%

PURPOSE

Sunscreen

Use:
Helps prevent sunburn.
If used as directed with other sun protection measures
(see directions), decreases the risk of skin cancer and
early skin ageing caused by the sun.

WARNINGS

FOR EXTERNAL USE ONLY

Skin Cancer/Skin Aging Alert: Spending time in the sun
increases your risk of skin cancer and early skin aging.
This product has been shown only to help prevent
sunburn, not skin cancer or early skin aging

Do not use on damaged or broken skin

When using this product: Keep out of eyes. Rinse with
water to remove

STOP USE

if rashes occur

KEEP OUT OF REACH OF CHILDREN

If product is swallowed,
get medical help or cont act a Poison Control Center right
away

Directions:
Apply generously 15 minutes before sun exposure.
Use a water-resistant sunscreen if swimming or sweating.
Reapply immediately after towel drying.
Reapply at least every 2 hours.
Children under 6 months of age: Ask a doctor

OTHER SAFETY INFORMATION

Sun Protection Measures:
Spending time in the sun increases your risk of skin cancer
and early skin aging. To decrease this risk, regularly use a
sunscreen with a Broad Spectrum SPF value of 15 or
higher and other sun protection measures including:
Limit time in the sun, especially from 10.00AM-2.00PM
Wear long-sleeved shirts, pants, hats, and sunglasses

INACTIVE INGREDIENT

Camellia Sinensis Leaf Extract, Carbomer,
Cetearyl alcohol, Cetearyl glucoside, Dimethicone,
Gluconolactone, Mica, Octyldodecanol, Potassium cetyl
phosphate, Purified water, Sodium Benzoate, Trolamine.

Other Information:
Protect the product in this container from excessive heat and
direct sun.

DESCRIPTION

THIS MULTI TASKING BODY SHIMMER,
MOISTURISER, AND SPF IN ONE
WILL LEAVE YOUR LIMBS GLOSSY, GOLDEN
AND SUMMER READY!